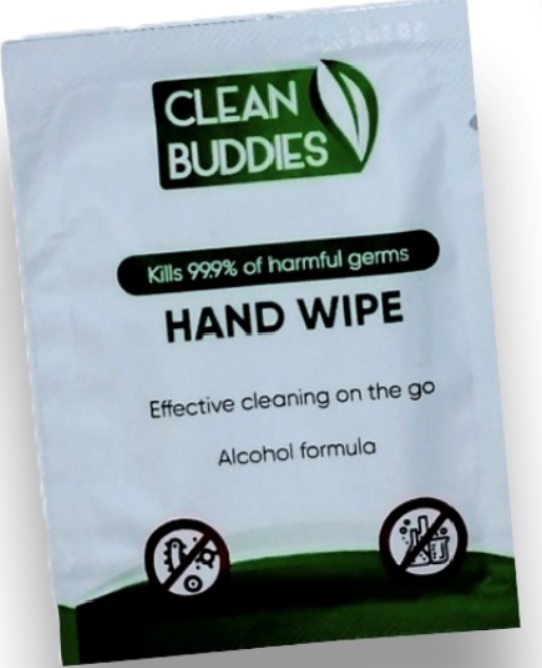 DRUG LABEL: CLEAN BUDDIES
NDC: 77658-002 | Form: CLOTH
Manufacturer: JUDITH ADORE TOBY LLC
Category: otc | Type: HUMAN OTC DRUG LABEL
Date: 20231221

ACTIVE INGREDIENTS: ISOPROPYL ALCOHOL 7.5 mL/1 1
INACTIVE INGREDIENTS: WATER

CLEAN BUDDIES

Active Ingredient

Isopropyl Alcohol 75%

Purpose

Antiseptic,

Uses

Hand Sanitizer wipe to help reduce bacteria that potentially can cause disease. For use when soap and water are not available.

Warnings

For external use only. Flammable. Keep away from heat or flame.

Do not use

- in children less than 2 months of age
- on open skin wounds
- When using this productkeep out of eyes, ears, and mouth. In case of contact with eyes, rinse eyes thoroughly with water.
- Stop use and ask a doctorif irritation or rash occurs. These may be signs of a serious condition.

Keep out of reach of children.

If swallowed, get medical help or contact a Poison Control Center right away.

Directions

- Apply wipe thoroughly to hands as desired.Allow with hands to dry.
- Dispose of used wipes in trash receptacle after use.Do not flush.

Other information

- Store between 15-30C (59-86F)
- Avoid freezing and excessive heat above 40C (104F)

Inactive Ingredient

Purified Water USP